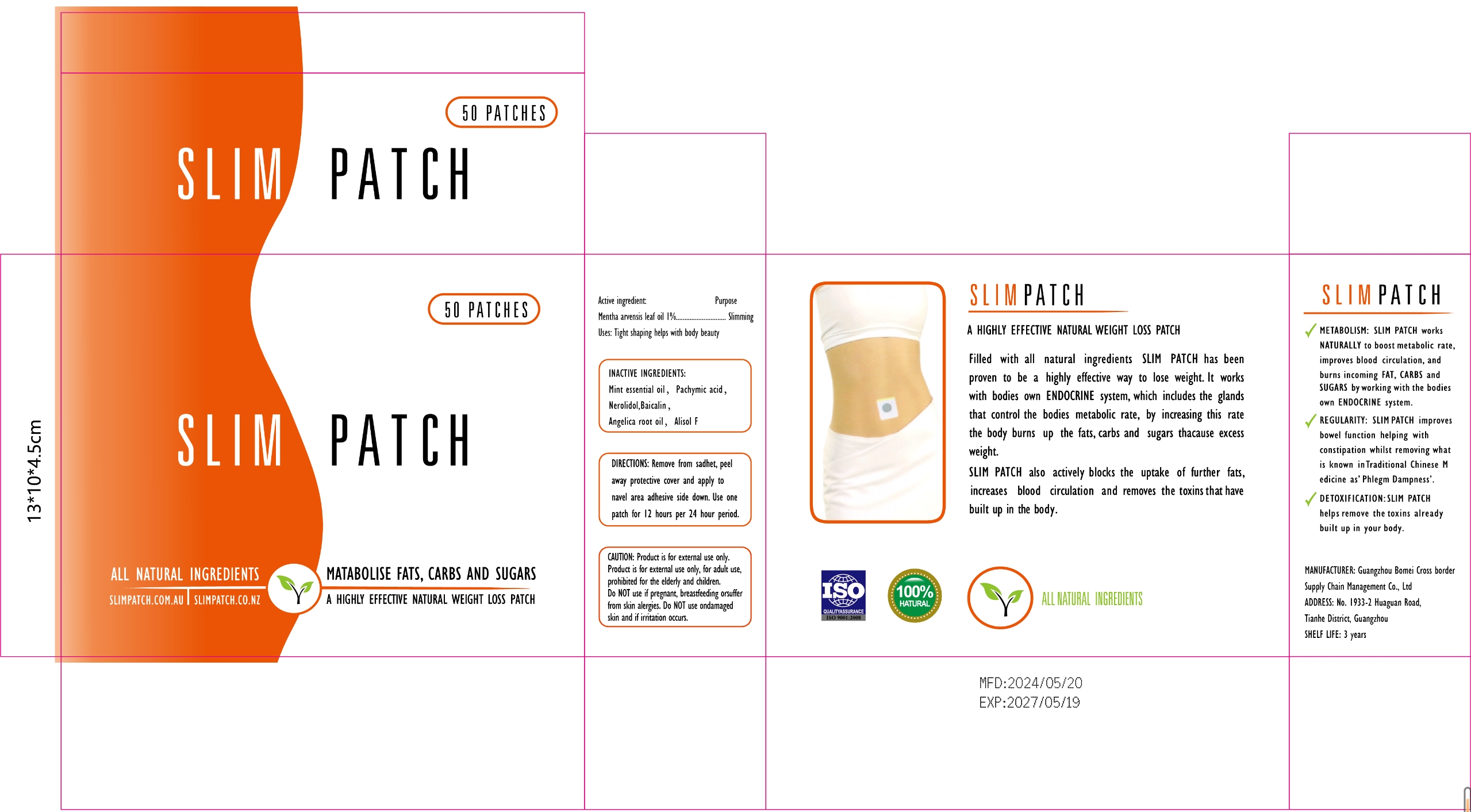 DRUG LABEL: SLIM Patch
NDC: 84537-001 | Form: PATCH
Manufacturer: Guangzhou Bomei Cross border Supply Chain Management Co., Ltd
Category: otc | Type: HUMAN OTC DRUG LABEL
Date: 20240714

ACTIVE INGREDIENTS: MENTHA ARVENSIS LEAF OIL 1 g/100 1
INACTIVE INGREDIENTS: PACHYMIC ACID; ALISOL F; ANGELICA ROOT OIL; BAICALIN; NEROLIDOL

SLIM PATCH

ACTIVE INGREDIENT

MENTHA ARVENSIS LEAF OIL 1%

PURPOSE

Slimming

KEEP OUT OF REACH OF CHILDREN SECTION

INDICATIONS AND USAGE

Tight shaping helps with body beauty

WARNINGS

CAUTlON: Product is for external use only.Product is for external use only, for adult use,prohibited for the elderly and children.Do NOT use if pregnant, breastfeeding orsufferfrom skin alergies. Do NOT use ondamagedskin and if irritation occurs.

DOSAGE AND ADMINISTRATION

DIRECTIONS: Remove from sadhet, peelaway protective cover and apply tonavel area adhesive side down. Use onepatch for 12 hours per 24 hour period.

STORAGE AND HANDLING

Store in a cool and shady place

INACTIVE INGREDIENT

PACHYMIC ACID
NEROLIDOL
BAICALIN
ANGELICA ROOT OIL
ALISOL F